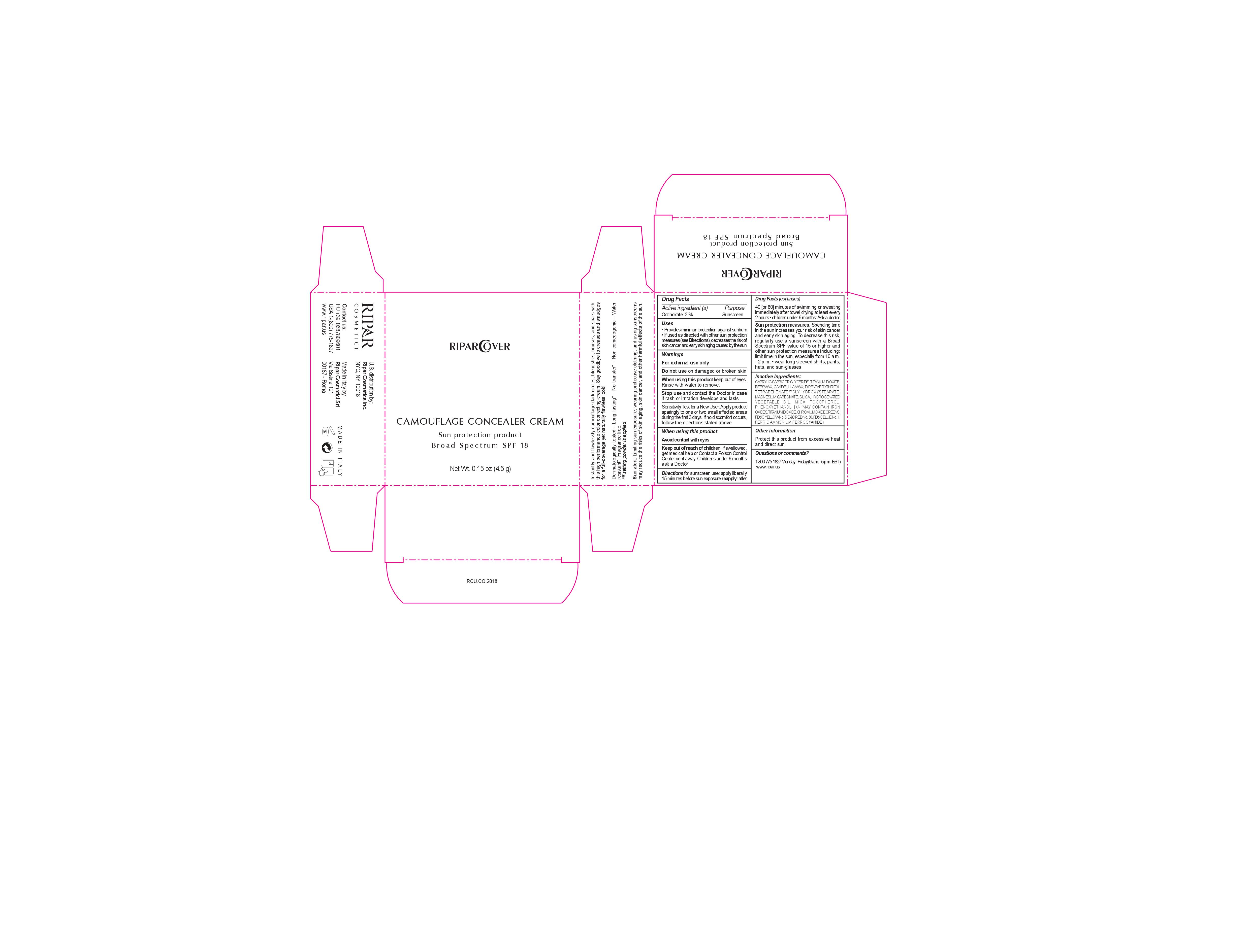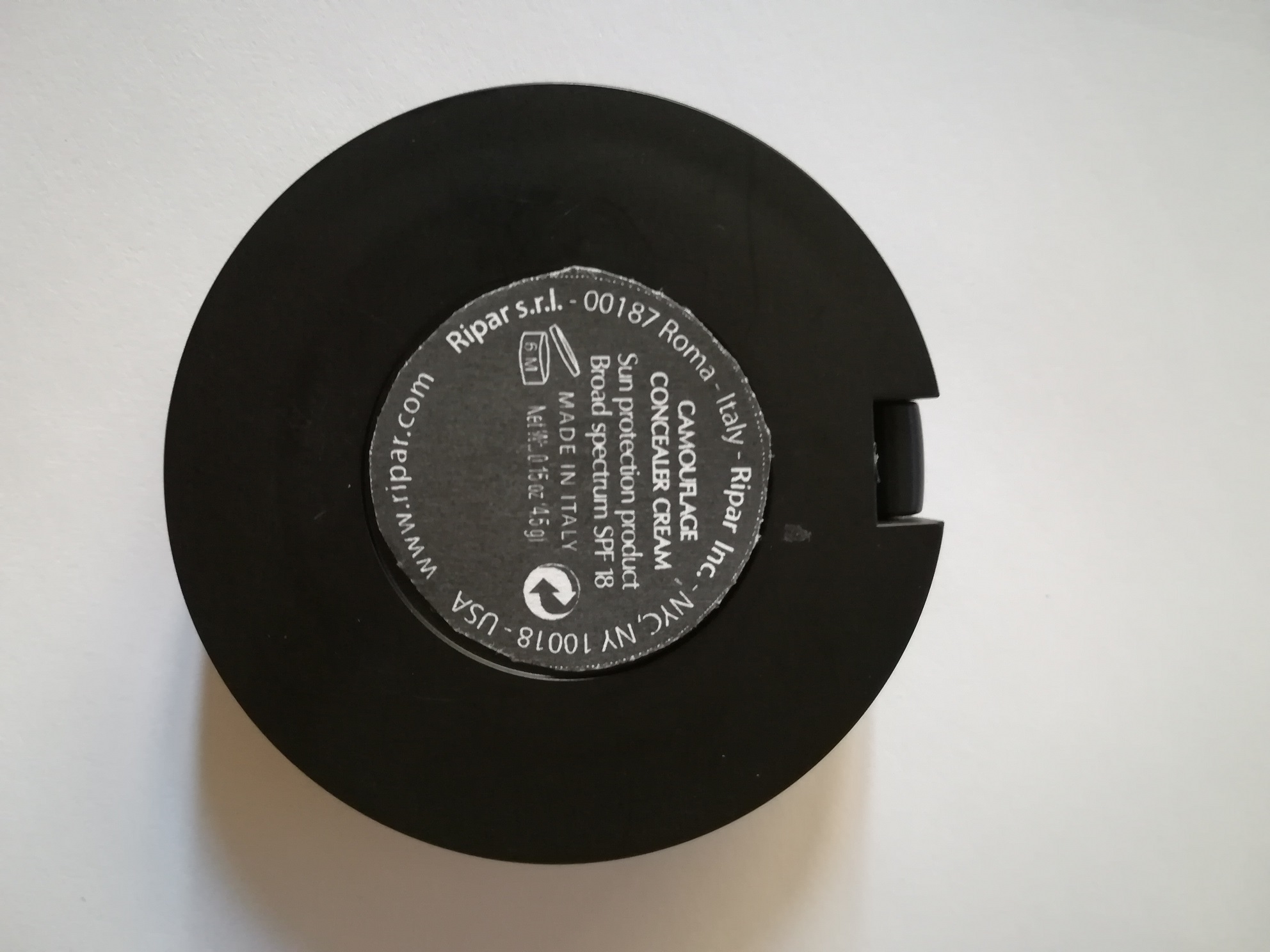 DRUG LABEL: Camouflage Concealer Cream
NDC: 72399-103 | Form: CREAM
Manufacturer: Ripar Cosmetici srl
Category: otc | Type: HUMAN OTC DRUG LABEL
Date: 20181007

ACTIVE INGREDIENTS: OCTINOXATE 2 mg/1 mL
INACTIVE INGREDIENTS: MEDIUM-CHAIN TRIGLYCERIDES; YELLOW WAX; CANDELILLA WAX; DIPENTAERYTHRITYL TRI-POLYHYDROXYSTEARATE; MAGNESIUM CARBONATE; SILICON DIOXIDE; HYDROGENATED PALM OIL; MICA; TOCOPHEROL; FERRIC OXIDE YELLOW; TITANIUM DIOXIDE; PHENOXYETHANOL; D&C RED NO. 36; FERRIC OXIDE RED

Camouflage Concealer Cream

ACTIVE INGREDIENTS PURPOSE

Oxtinoxate 2% sunscreen

Warnings

SUN ALERT: Limiting sun exposures, wearing protective clothing and using sunscreens may reduce the risks of skin aging. skin cancer, and other harmful effects of the sun

For external use only.

Do not use on damaged or broken skin.

When using this product keep our of the eyes. Rinse with water to remove.

SUN PROTECTION MEASURES. Spending times in the sun increases your risk of skin cancer and early skin aging. To decrease this risk, regularly use a sunscreen with a broad Spectrum SPF value 15 or higher and other sun protection measures including: limit time to the sun especially from 10:00 am to 2:00 pm. Weat long sleeve shirts , pants, hats and sunglasses

DIscontinue uses if signs or irritationsor rash appears. If irritation or rash persists, consult with a doctor.

Keep out of reach of children. If swallowed, get medical help or Contact Poison Control Central right away

Children under 6 months ask a doctor

WARNINGS

Children under 6 months: ask a doctor

Warnings

Keep out of reach of children

Questions or comments?

1- 800-775-1827. M-F 9:00 am to 5:00 pm EST

www.ripar.us

Other Information

Protect this product from excessive heat and direct sun

Directions

- provides minimun protection against sunburn
- if used as directed with other sun protection measures (see directions), decreases the risks of skin cancer and early skin aging caused by the sun

DOSAGE AND ADMINISTRATION

- apply liberally 15 minutes before sun exposure reapply adter 40 or 80 minutes of swimming or sweating immediately after towel drying at least every 2 hours
- children under 6 months of age, consult with a doctor

Uses

- provides minimun protection against sunburn
- if used as directed with other sun protection measures (see directions), decreases the risks of skin cancer and early skin aging caused by the sun

Inactive Ingredients

CAPRYLIC/CAPRIC TRIGLYCERIDE, MEDIUM CHAIN TRIGLYCERIDES, BEESWAX YELLOW WAX, CANDELILLA WAX, OCTINOXATE, DIPENTAERYTHRITYL TRI-POLYHYDROXYSTEARATE, MAGNESIUM CARBONATE, SILICON DIOXIDE, HYDROGENATED PALM, MICA, TOCOPHEROL , PHENOXYETHANOL, FERRIC OXIDE YELLOW , FERRIC OXIDE RED, TITANIUM DIOXIDE, D&C RED No. 36

Uses

- provides minimun protection against sunburn
- if used as directed with other sun protection measures (see directions), decreases the risks of skin cancer and early skin aging caused by the sun